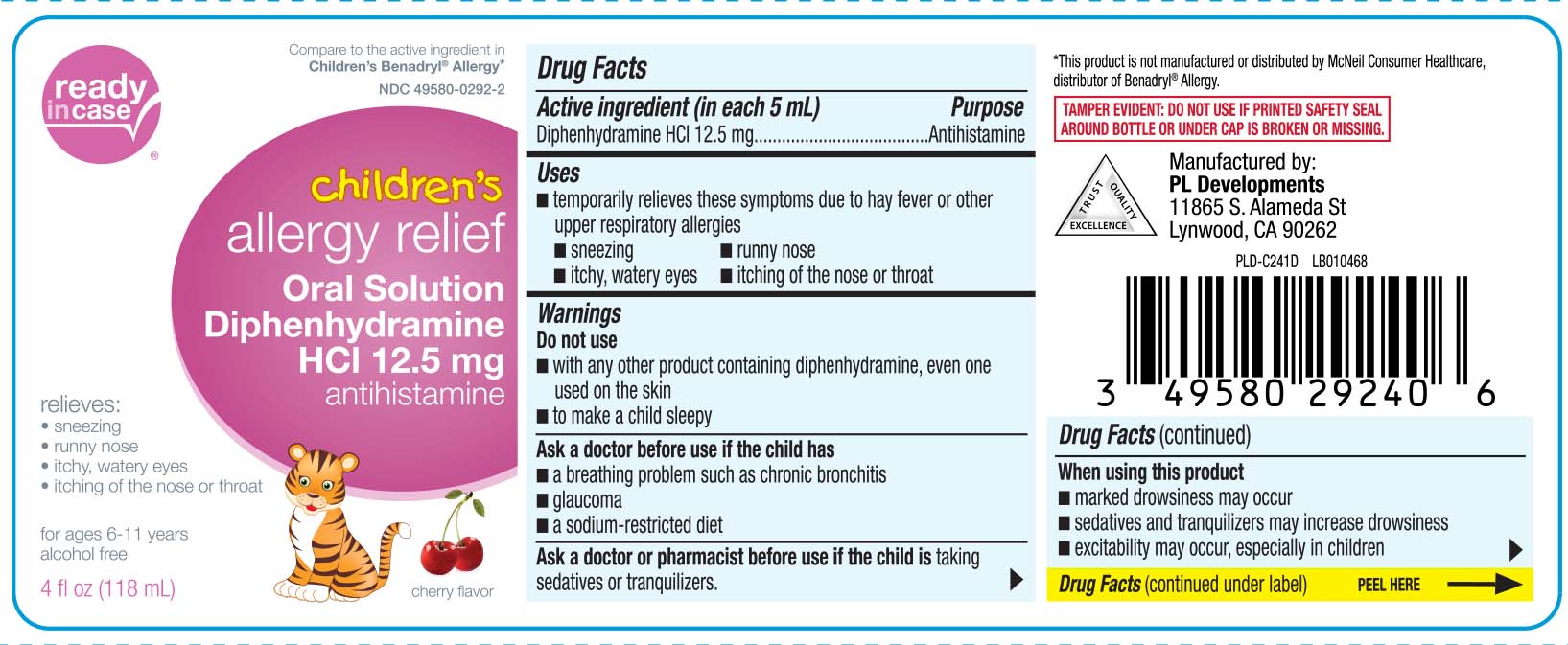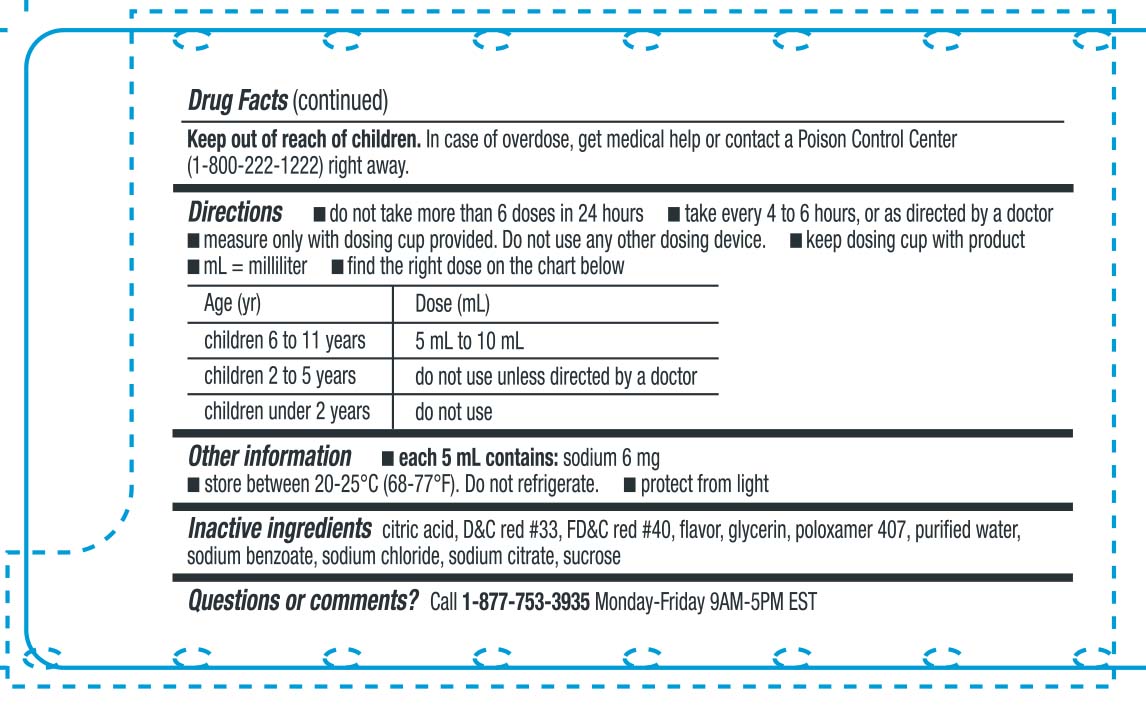 DRUG LABEL: Childrens Allergy
NDC: 49580-0292 | Form: LIQUID
Manufacturer: P & L Development, LLC
Category: otc | Type: HUMAN OTC DRUG LABEL
Date: 20250530

ACTIVE INGREDIENTS: DIPHENHYDRAMINE HYDROCHLORIDE 12.5 mg/5 mL
INACTIVE INGREDIENTS: ANHYDROUS CITRIC ACID; GLYCERIN; POLOXAMER 407; WATER; SODIUM BENZOATE; SODIUM CHLORIDE; TRISODIUM CITRATE DIHYDRATE; SUCROSE; D&C RED NO. 33; FD&C RED NO. 40

Drug Facts

Active ingredient (in each 5 mL)

Diphenhydramine HCl 12.5 mg

Purpose

Antihistamine

Uses

- temporarily relieves these symptoms due to hay fever or other upper respiratory allergies:
  - runny nose
  - sneezing
  - itchy, watery eyes
  - itching of the nose or throat

Warnings

Do not use

- to make a child sleepy
- with any other product containing diphenhydramine, even one used on skin

Ask a doctor before use if the child has

- glaucoma
- a breathing problem such as chronic bronchitis
- a sodium-restricted diet

Ask a doctor or pharmacist before use if the child is

taking sedatives or tranquilizers.

When using this product

- marked drowsiness may occur
- sedatives and tranquilizers may increase drowsiness
- excitability may occur, especially in children

Keep out of the reach of children.

In case of overdose, get medical help or contact a Poison Control Center (1-800-222-1222) right away.

Directions

- do not take more than 6 doses in 24 hours
- take every 4 to 6 hours, or as directed by a doctor
- measure only with dosing cup provided. Do not use any other dosing device.
- mL = milliliter
- keep dosing cup with product
- find the right dose on the chart below

Age (yrs) | Dose (mL)
children 6 to 11 years | 5 mL to 10 mL
children 2 to 5 years | do not use unless directed by a doctor
children under 2 years | do not use

Other information

- each 5 mL contains: sodium 6 mg
- store between 20-25ºC (68-77F). Do not refrigerate.
- Protect from light.

Inactive ingredients

citric acid, D&C red #33, FD&C red #40 flavors, glycerin, poloxamer 407, purified water, sodium benzoate, sodium chloride, sodium citrate, sucrose

Questions or comments?

Call 1-877-753-3935 Monday-Friday 9AM-5PM EST

Principal Display Panel

Compare to the active ingredient Children's Benadryl® Allergy*

Children's

allergy relief

Oral Solution

Diphenhydramine HCl 12.5 mg

antihistamine

relieves:

- sneezing
- running nose
- itchy, watery eyes
- itching of the nose or throat

for ages 6 to 11

alcohol free

cherry flavor

FL OZ (mL)

*This product is not manufactured or distributed b McNeil Consumer Healthcare, distributor of Benadryl® Allergy

TAMPER EVIDENT: DO NOT USE IF PRINTED SAFETY SEAL AROUND BOTTLE OR UNDER CAP IS BROKEN OR MISSING.

Manufactured by:

PL Developmnets

11865 S. Alameda St

Lynwood, CA 90262

Package Label

Children's Allergy Relief Diphenhydramine HCl 12.5 mg Cherry Flavor
Children's Allergy Relief Diphenhydramine HCl 12.5 mg Cherry Flavor